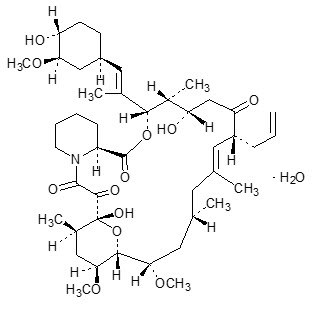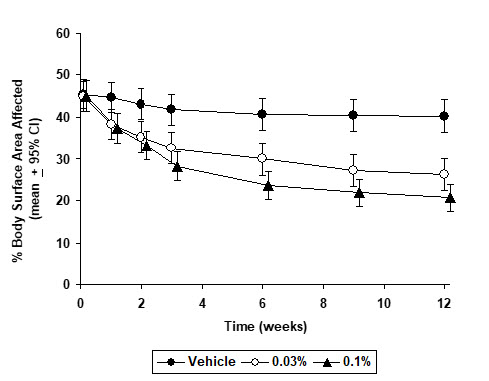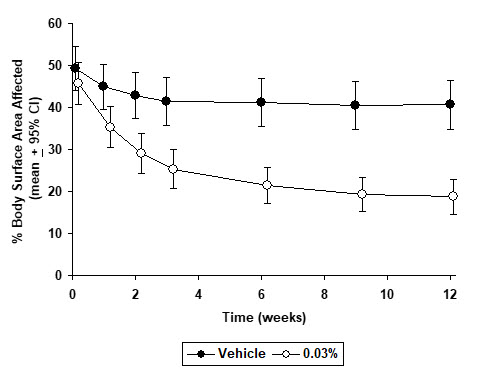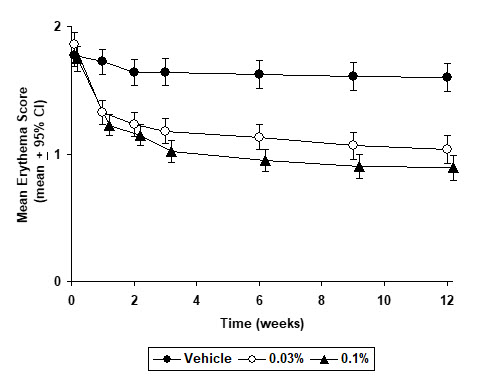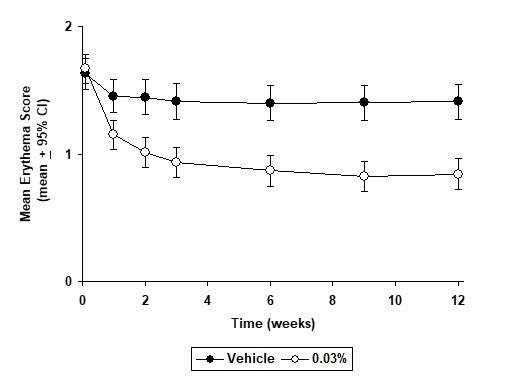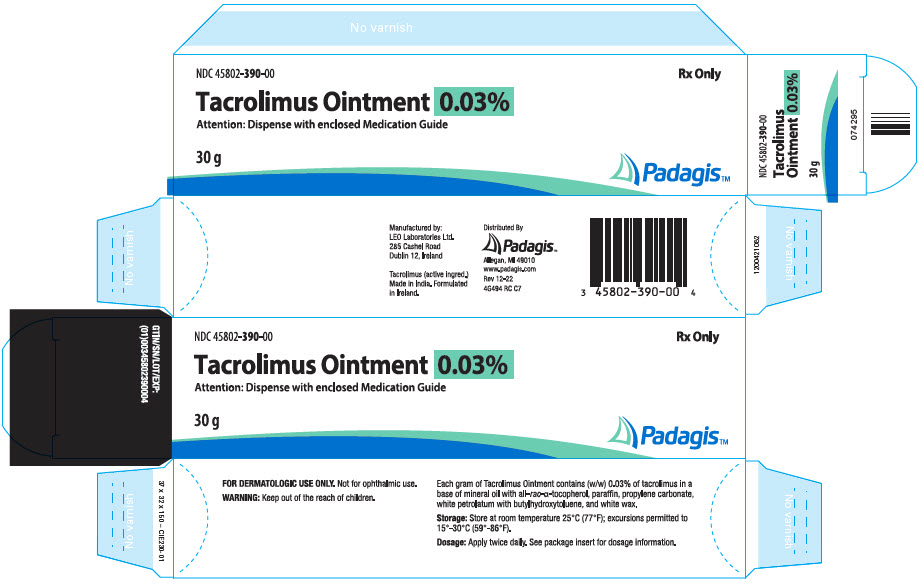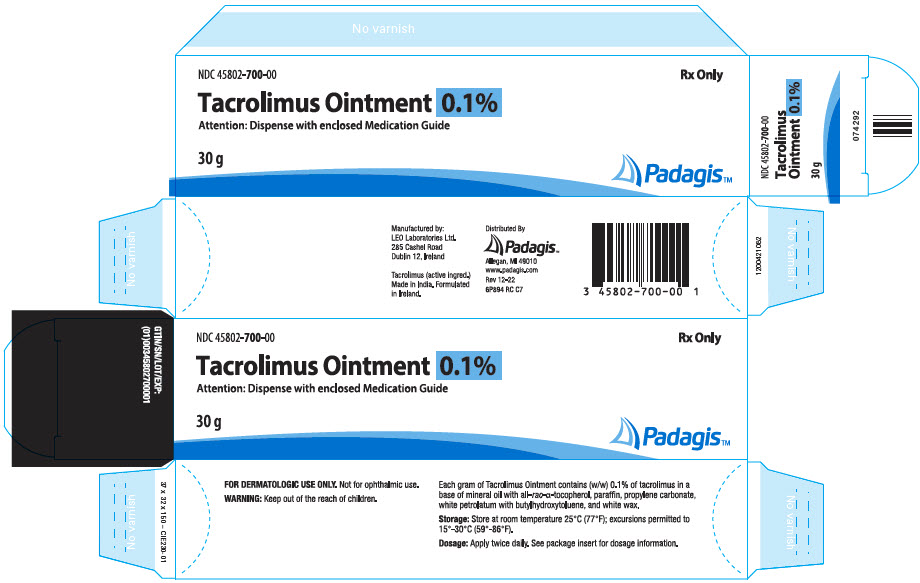 DRUG LABEL: Tacrolimus
NDC: 45802-390 | Form: OINTMENT
Manufacturer: Padagis Israel Pharmaceuticals Ltd
Category: prescription | Type: HUMAN PRESCRIPTION DRUG LABEL
Date: 20211115

ACTIVE INGREDIENTS: TACROLIMUS 0.3 mg/1 g
INACTIVE INGREDIENTS: MINERAL OIL; PARAFFIN; PROPYLENE CARBONATE; PETROLATUM; WHITE WAX; .ALPHA.-TOCOPHEROL, DL-; BUTYLATED HYDROXYTOLUENE

Tacrolimus
Ointment 0.03%
Ointment 0.1%

FOR DERMATOLOGIC USE ONLY
NOT FOR OPHTHALMIC USE

Rx Only

Prescribing Information

See boxed WARNING concerning long-term safety of topical calcineurin inhibitors

DESCRIPTION

Tacrolimus Ointment contains tacrolimus, a macrolide immunosuppressant produced by Streptomyces tsukubaensis. It is for topical dermatologic use only. Chemically, tacrolimus is designated as [3S-[3R*[E(1S*,3S*,4S*)],4S*,5R*,8S*,9E,12R*,14R*,15S*,16R*,18S*,19S*,26aR*]]-5,6,8,11,12,13,14,15,16,17,18,19,24,25,26,26a-hexadecahydro-5,19-dihydroxy-3-[2-(4-hydroxy-3-methoxycyclohexyl)-1-methylethenyl]-14,16-dimethoxy-4,10, 12,18-tetramethyl-8-(2-propenyl)-15,19-epoxy-3H-pyrido[2,1-c][1,4] oxaazacyclotricosine-1,7,20,21(4H,23H)-tetrone,monohydrate. It has the following structural formula:

Tacrolimus has an empirical formula of C44H69NO12∙H2O and a formula weight of 822.03. Each gram of Tacrolimus Ointment contains (w/w) either 0.03% or 0.1% of tacrolimus in a base of mineral oil with all-rac-α-tocopherol, paraffin, propylene carbonate, white petrolatum with butylhydroxytoluene, and white wax.

CLINICAL PHARMACOLOGY

Mechanism of Action

The mechanism of action of tacrolimus in atopic dermatitis is not known. While the following have been observed, the clinical significance of these observations in atopic dermatitis is not known. It has been demonstrated that tacrolimus inhibits T-lymphocyte activation by first binding to an intracellular protein, FKBP-12. A complex of tacrolimus-FKBP-12, calcium, calmodulin, and calcineurin is then formed and the phosphatase activity of calcineurin is inhibited. This effect has been shown to prevent the dephosphorylation and translocation of nuclear factor of activated T-cells (NF-AT), a nuclear component thought to initiate gene transcription for the formation of lymphokines (such as interleukin-2, gamma interferon). Tacrolimus also inhibits the transcription for genes which encode IL-3, IL-4, IL-5, GM-CSF, and TNF-α, all of which are involved in the early stages of T-cell activation. Additionally, tacrolimus has been shown to inhibit the release of pre-formed mediators from skin mast cells and basophils, and to down regulate the expression of FcɛRI on Langerhans cells.

Pharmacokinetics

Absorption

The pooled results from three pharmacokinetic studies in 88 adult atopic dermatitis patients indicate that tacrolimus is minimally absorbed after the topical application of Tacrolimus Ointment. Peak tacrolimus blood concentrations ranged from undetectable to 20 ng/mL after single or multiple doses of 0.03% and 0.1% Tacrolimus Ointment, with 85% (75/88) of the patients having peak blood concentrations less than 2 ng/mL. In general as treatment continued, systemic exposure declined as the skin returned to normal. In clinical studies with periodic blood sampling, a similar distribution of tacrolimus blood levels was also observed in adult patients, with 90% (1253/1391) of patients having a blood concentration less than 2 ng/mL.

The absolute bioavailability of tacrolimus from Tacrolimus Ointment in atopic dermatitis patients is approximately 0.5%. In adults with an average of 53% BSA treated, exposure (AUC) of tacrolimus from Tacrolimus Ointment is approximately 30-fold less than that seen with oral immunosuppressive doses in kidney and liver transplant patients.

Mean peak tacrolimus blood concentrations following oral administration (0.3 mg/kg/day) in adult kidney transplant (n=26) and liver transplant (n=17) patients are 24.2±15.8 ng/mL and 68.5±30.0 ng/mL, respectively. The lowest tacrolimus blood level at which systemic effects (e.g., immunosuppression) can be observed is not known.

Systemic levels of tacrolimus have also been measured in pediatric patients (see Special Populations: Pediatrics).

Distribution

The plasma protein binding of tacrolimus is approximately 99% and is independent of concentration over a range of 5-50 ng/mL. Tacrolimus is bound mainly to albumin and alpha-1-acid glycoprotein, and has a high level of association with erythrocytes. The distribution of tacrolimus between whole blood and plasma depends on several factors, such as hematocrit, temperature at the time of plasma separation, drug concentration, and plasma protein concentration. In a US study, the ratio of whole blood concentration to plasma concentration averaged 35 (range 12 to 67).

There was no evidence based on blood concentrations that tacrolimus accumulates systemically upon intermittent topical application for periods of up to 1 year. As with other topical calcineurin inhibitors, it is not known whether tacrolimus is distributed into the lymphatic system.

Metabolism

Tacrolimus is extensively metabolized by the mixed-function oxidase system, primarily the cytochrome P-450 system (CYP3A). A metabolic pathway leading to the formation of 8 possible metabolites has been proposed. Demethylation and hydroxylation were identified as the primary mechanisms of biotransformation in vitro. The major metabolite identified in incubations with human liver microsomes is 13-demethyl tacrolimus. In in vitro studies, a 31-demethyl metabolite has been reported to have the same activity as tacrolimus.

Excretion

The mean clearance following IV administration of tacrolimus is 0.040, 0.083 and 0.053 L/hr/kg in healthy volunteers, adult kidney transplant patients and adult liver transplant patients, respectively. In man, less than 1% of the dose administered is excreted unchanged in urine.

In a mass balance study of IV administered radiolabeled tacrolimus to 6 healthy volunteers, the mean recovery of radiolabel was 77.8 ± 12.7%. Fecal elimination accounted for 92.4 ± 1.0% and the elimination half-life based on radioactivity was 48.1 ± 15.9 hours whereas it was 43.5 ± 11.6 hours based on tacrolimus concentrations. The mean clearance of radiolabel was 0.029 ± 0.015 L/hr/kg and clearance of tacrolimus was 0.029 ± 0.009 L/hr/kg.

When administered PO, the mean recovery of the radiolabel was 94.9 ± 30.7%. Fecal elimination accounted for 92.6 ± 30.7%, urinary elimination accounted for 2.3 ± 1.1% and the elimination half-life based on radioactivity was 31.9 ± 10.5 hours whereas it was 48.4 ± 12.3 hours based on tacrolimus concentrations. The mean clearance of radiolabel was 0.226 ± 0.116 L/hr/kg and clearance of tacrolimus 0.172 ± 0.088 L/hr/kg.

Special Populations

Pediatrics

In a pharmacokinetic study of 14 pediatric atopic dermatitis patients, between the ages of 2-5 years, peak blood concentrations of tacrolimus ranged from undetectable to 14.8 ng/mL after single or multiple doses of 0.03% Tacrolimus Ointment, with 86% (12/14) of patients having peak blood concentrations below 2 ng/mL throughout the study.

The highest peak concentration was observed in one patient with 82% BSA involvement on day 1 following application of 0.03% Tacrolimus Ointment. The peak concentrations for this subject were 14.8 ng/mL on day 1 and 4.1 ng/mL on day 14. Mean peak tacrolimus blood concentrations following oral administration in pediatric liver transplant patients (n = 9) were 48.4 ± 27.9 ng/mL.

In a similar pharmacokinetic study with 61 enrolled pediatric patients (ages 6-12 years) with atopic dermatitis, peak tacrolimus blood concentrations ranged from undetectable to 5.3 ng/mL after single or multiple doses of 0.1% Tacrolimus Ointment, with 91% (52/57) of evaluable patients having peak blood concentrations below 2 ng/mL throughout the study period. When detected, systemic exposure generally declined as treatment continued.

In clinical studies with periodic blood sampling, a similar distribution of tacrolimus blood levels was also observed, with 98% (509/522) of pediatric patients having a blood concentration below 2 ng/mL.

Renal Insufficiency

The effect of renal insufficiency on the pharmacokinetics of topically administered tacrolimus has not been evaluated. The mean clearance of IV administered tacrolimus in patients with renal dysfunction was similar to that of normal volunteers. On the basis of this information dose-adjustment is not expected to be needed.

Hepatic Insufficiency

The effect of hepatic insufficiency on the pharmacokinetics of topically administered tacrolimus has not been evaluated but dose-adjustment is not expected to be needed.

CLINICAL STUDIES

Three randomized, double-blind, vehicle-controlled, multi-center, phase 3 studies were conducted to evaluate Tacrolimus Ointment for the treatment of patients with moderate to severe atopic dermatitis. One (Pediatric) study included 351 patients 2-15 years of age, and the other two (Adult) studies included a total of 632 patients 15-79 years of age. Fifty-five percent (55%) of the patients were women and 27% were black. At baseline, 58% of the patients had severe disease and the mean body surface area (BSA) affected was 46%. Over 80% of patients had atopic dermatitis affecting the face and/or neck region. In these studies, patients applied either Tacrolimus Ointment 0.03%, Tacrolimus Ointment 0.1%, or vehicle ointment twice daily to 10% - 100% of their BSA for up to 12 weeks.

In the pediatric study, a significantly greater (p < 0.001) percentage of patients achieved at least 90% improvement based on the physician's global evaluation of clinical response (the pre-defined primary efficacy endpoint) in the Tacrolimus Ointment 0.03% treatment group compared to the vehicle treatment group, but there was insufficient evidence that Tacrolimus Ointment 0.1% provided more efficacy than Tacrolimus Ointment 0.03%.

In both adult studies, a significantly greater (p < 0.001) percentage of patients achieved at least 90% improvement based on the physician's global evaluation of clinical response in the Tacrolimus Ointment 0.03% and Tacrolimus Ointment 0.1% treatment groups compared to the vehicle treatment group. There was evidence that Tacrolimus Ointment 0.1% may provide more efficacy than Tacrolimus Ointment 0.03%. The difference in efficacy between Tacrolimus Ointment 0.1% and 0.03% was particularly evident in adult patients with severe disease at baseline, adults with extensive BSA involvement, and black adults. Response rates for each treatment group are shown below by age groups. Because the two adult studies were identically designed, the results from these studies were pooled in this table.

Global Improvement over Baseline at the End-Of-Treatment in Three Phase 3 Studies
Physician's Global Evaluation of Clinical Response (% Improvement) | Pediatric Study (2-15 Years of Age) |  | Adult Studies
Physician's Global Evaluation of Clinical Response (% Improvement) | Vehicle Ointment | Tacrolimus Ointment 0.03% | Vehicle Ointment | Tacrolimus Ointment 0.03% | Tacrolimus Ointment 0.1%
Physician's Global Evaluation of Clinical Response (% Improvement) | N = 116 | N = 117 | N = 212 | N = 211 | N = 209
100% | 4 (3%) | 14 (12%) | 2 (1%) | 21 (10%) | 20 (10%)
≥ 90% | 8 (7%) | 42 (36%) | 14 (7%) | 58 (28%) | 77 (37%)
≥ 75% | 18 (16%) | 65 (56%) | 30 (14%) | 97 (46%) | 117 (56%)
≥ 50% | 31 (27%) | 85 (73%) | 42 (20%) | 130 (62%) | 152 (73%)

A statistically significant difference in the percentage of adult patients with ≥ 90% improvement was achieved by week 1 for those treated with Tacrolimus Ointment 0.1%, and by week 3 for those treated with Tacrolimus Ointment 0.03%. A statistically significant difference in the percentage of pediatric patients with ≥ 90% improvement was achieved by week 2 for those treated with Tacrolimus Ointment 0.03%.

In adult patients who had achieved ≥ 90% improvement at the end of treatment, 35% of those treated with Tacrolimus Ointment 0.03% and 41% of those treated with Tacrolimus Ointment 0.1%, regressed from this state of improvement at 2 weeks after end-of-treatment. In pediatric patients who had achieved ≥ 90% improvement, 54% of those treated with Tacrolimus Ointment 0.03% regressed from this state of improvement at 2 weeks after end-of-treatment. Because patients were not followed for longer than 2 weeks after end-of-treatment, it is not known how many additional patients regressed at periods longer than 2 weeks after cessation of therapy.

In both Tacrolimus Ointment treatment groups in adults and in the Tacrolimus Ointment 0.03% treatment group in pediatric patients, a significantly greater improvement compared to vehicle (p < 0.001) was observed in the secondary efficacy endpoints of percent body surface area involved, patient evaluation of pruritus, erythema, edema, excoriation, oozing, scaling, and lichenification. The following two graphs depict the time course of improvement in the percent body surface area affected in adult and in pediatric patients as a result of treatment.

Figure 1 - Adult Patients Body Surface Area Over Time

Figure 2 – Pediatric Patients Body Surface Area Over Time

The following two graphs depict the time course of improvement in erythema in adult and in pediatric patients as a result of treatment.

Figure 3 - Adult Patients Mean Erythema Over Time

Figure 4 - Pediatric Patients Mean Erythema Over Time

The time course of improvement in the remaining secondary efficacy variables was similar to that of erythema, with improvement in lichenification slightly slower.

INDICATIONS AND USAGE

Tacrolimus Ointment, both 0.03% and 0.1% for adults, and only 0.03% for children aged 2 to 15 years, is indicated as second-line therapy for the short-term and non-continuous chronic treatment of moderate to severe atopic dermatitis in non-immunocompromised adults and children who have failed to respond adequately to other topical prescription treatments for atopic dermatitis, or when those treatments are not advisable.

Tacrolimus Ointment is not indicated for children younger than 2 years of age (see boxed WARNING, WARNINGS and PRECAUTIONS: Pediatric Use).

CONTRAINDICATIONS

Tacrolimus Ointment is contraindicated in patients with a history of hypersensitivity to tacrolimus or any other component of the ointment.

WARNINGS

WARNING

Long-term Safety of Topical Calcineurin Inhibitors Has Not Been Established
Although a causal relationship has not been established, rare cases of malignancy (e.g., skin and lymphoma) have been reported in patients treated with topical calcineurin inhibitors, including Tacrolimus Ointment.
Therefore:

- Continuous long-term use of topical calcineurin inhibitors, including Tacrolimus Ointment, in any age group should be avoided, and application limited to areas of involvement with atopic dermatitis.
- Tacrolimus Ointment is not indicated for use in children less than 2 years of age. Only 0.03% Tacrolimus Ointment is indicated for use in children 2-15 years of age.

Prolonged systemic use of calcineurin inhibitors for sustained immunosuppression in animal studies and transplant patients following systemic administration has been associated with an increased risk of infections, lymphomas, and skin malignancies. These risks are associated with the intensity and duration of immunosuppression.

Based on the information above and the mechanism of action, there is a concern about potential risk with the use of topical calcineurin inhibitors, including Tacrolimus Ointment. While a causal relationship has not been established, rare cases of skin malignancy and lymphoma have been reported in patients treated with topical calcineurin inhibitors, including Tacrolimus Ointment. Therefore:

- Tacrolimus Ointment should not be used in immunocompromised adults and children.
- If signs and symptoms of atopic dermatitis do not improve within 6 weeks, patients should be re-examined by their healthcare provider and their diagnosis be confirmed (see PRECAUTIONS: General).
- The safety of Tacrolimus Ointment has not been established beyond one year of non-continuous use.

(See CLINICAL PHARMACOLOGY, boxed WARNING, INDICATIONS AND USAGE, and DOSAGE AND ADMINISTRATION).

PRECAUTIONS

General

The use of Tacrolimus Ointment should be avoided on pre-malignant and malignant skin conditions. Some malignant skin conditions, such as cutaneous T-cell lymphoma (CTCL), may mimic atopic dermatitis.

The use of tacrolimus ointment is not recommended in patients having skin conditions with a skin barrier defect where there is the potential for increased systemic absorption of tacrolimus, including but not limited to, Netherton's syndrome, lamellar ichthyosis, generalized erythroderma or cutaneous Graft Versus Host Disease. Oral application is also not recommended. Post-marketing cases of increased tacrolimus blood level have been reported in these conditions.

The use of Tacrolimus Ointment may cause local symptoms such as skin burning (burning sensation, stinging, soreness) or pruritus. Localized symptoms are most common during the first few days of Tacrolimus Ointment application and typically improve as the lesions of atopic dermatitis resolve. With Tacrolimus Ointment 0.1%, 90% of the skin burning events had a duration between 2 minutes and 3 hours (median 15 minutes). 90% of the pruritus events had a duration between 3 minutes and 10 hours (median 20 minutes) (see ADVERSE REACTIONS).

Bacterial and Viral Skin Infections

Before commencing treatment with Tacrolimus Ointment, cutaneous bacterial or viral infections at treatment sites should be resolved. Studies have not evaluated the safety and efficacy of Tacrolimus Ointment in the treatment of clinically infected atopic dermatitis.

While patients with atopic dermatitis are predisposed to superficial skin infections including eczema herpeticum (Kaposi's varicelliform eruption), treatment with Tacrolimus Ointment may be independently associated with an increased risk of varicella zoster virus infection (chicken pox or shingles), herpes simplex virus infection, or eczema herpeticum.

Patients with Lymphadenopathy

In clinical studies, 112/13494 (0.8%) cases of lymphadenopathy were reported and were usually related to infections (particularly of the skin) and noted to resolve upon appropriate antibiotic therapy. Of these 112 cases, the majority had either a clear etiology or were known to resolve. Transplant patients receiving immunosuppressive regimens (e.g., systemic tacrolimus) are at increased risk for developing lymphoma; therefore, patients who receive Tacrolimus Ointment and who develop lymphadenopathy should have the etiology of their lymphadenopathy investigated. In the absence of a clear etiology for the lymphadenopathy, or in the presence of acute infectious mononucleosis, Tacrolimus Ointment should be discontinued. Patients who develop lymphadenopathy should be monitored to ensure that the lymphadenopathy resolves.

Sun Exposure

During the course of treatment, patients should minimize or avoid natural or artificial sunlight exposure, even while Tacrolimus Ointment is not on the skin. It is not known whether Tacrolimus Ointment interferes with skin response to ultraviolet damage.

Immunocompromised Patients

The safety and efficacy of Tacrolimus Ointment in immunocompromised patients have not been studied.

Renal Insufficiency

Rare post-marketing cases of acute renal failure have been reported in patients treated with Tacrolimus Ointment. Systemic absorption is more likely to occur in patients with epidermal barrier defects especially when Tacrolimus Ointment is applied to large body surface areas. Caution should also be exercised in patients predisposed to renal impairment.

Information for Patients

(See Medication Guide)

Patients using Tacrolimus Ointment should receive and understand the information in the Medication Guide. Please refer to the Medication Guide for providing instruction and information to the patient.

What is the most important information patients should know about Tacrolimus Ointment?

The safety of using Tacrolimus Ointment for a long period of time is not known. A very small number of people who have used Tacrolimus Ointment have had cancer (for example, skin or lymphoma). However, a link with Tacrolimus Ointment has not been shown. Because of this concern, instruct patients:

- Do not use Tacrolimus Ointment continuously for a long time.
- Use Tacrolimus Ointment only on areas of skin that have eczema.
- Do not use Tacrolimus Ointment on a child under 2 years old.

Tacrolimus Ointment comes in two strengths:

- Only Tacrolimus Ointment 0.03% is for use on children aged 2 to 15 years.
- Either Tacrolimus Ointment 0.03% or 0.1% can be used by adults and children 16 years and older.

Advise patients to talk to their prescriber for more information.

How should Tacrolimus Ointment be used?

Advise patients to:

- Use Tacrolimus Ointment exactly as prescribed.
- Use Tacrolimus Ointment only on areas of skin that have eczema.
- Use Tacrolimus Ointment for short periods, and if needed, treatment may be repeated with breaks in between.
- Stop Tacrolimus Ointment when the signs and symptoms of eczema, such as itching, rash, and redness go away, or as directed.
- Follow their doctor's advice if symptoms of eczema return after treatment with Tacrolimus Ointment.
- Call their doctor if:
  - Their symptoms get worse with Tacrolimus Ointment.
  - They get an infection on their skin.
  - Their symptoms do not improve after 6 weeks of treatment. Sometimes other skin diseases can look like eczema.

To apply Tacrolimus Ointment:

Advise patients:

- Wash their hands before applying Tacrolimus Ointment.
- Apply a thin layer of Tacrolimus Ointment twice daily to the areas of skin affected by eczema.
- Use the smallest amount of Tacrolimus Ointment needed to control the signs and symptoms of eczema.
- If they are a caregiver applying Tacrolimus Ointment to a patient, or if they are a patient who is not treating their hands, wash their hands with soap and water after applying Tacrolimus Ointment. This should remove any ointment left on the hands.
- Do not bathe, shower, or swim right after applying Tacrolimus Ointment. This could wash off the ointment.
- Moisturizers can be used with Tacrolimus Ointment. Make sure they check with their doctor first about the products that are right for them. Because the skin of patients with eczema can be very dry, it is important to keep up good skin care practices. If they use moisturizers, apply them after Tacrolimus Ointment.

What should patients avoid while using Tacrolimus Ointment?

Advise patients:

- Do not use ultraviolet light therapy, sun lamps, or tanning beds during treatment with Tacrolimus Ointment.
- Limit sun exposure during treatment with Tacrolimus Ointment even when the medicine is not on their skin. If patients need to be outdoors after applying Tacrolimus Ointment, wear loose fitting clothing that protects the treated area from the sun. Doctors should advise what other types of protection from the sun patients should use.
- Do not cover the skin being treated with bandages, dressings or wraps. Patients can wear normal clothing.
- Avoid getting Tacrolimus Ointment in the eyes or mouth. Do not swallow Tacrolimus Ointment. Patients should call their doctor if they swallow Tacrolimus Ointment.

Drug Interactions

Formal topical drug interaction studies with Tacrolimus Ointment have not been conducted. Based on its extent of absorption, interactions of Tacrolimus Ointment with systemically administered drugs are unlikely to occur but cannot be ruled out (see CLINICAL PHARMACOLOGY). The concomitant administration of known CYP3A4 inhibitors in patients with widespread and/or erythrodermic disease should be done with caution. Some examples of such drugs are erythromycin, itraconazole, ketoconazole, fluconazole, calcium channel blockers and cimetidine.

Carcinogenesis, Mutagenesis, Impairment of Fertility

No evidence of genotoxicity was seen in bacterial (Salmonella and E. coli) or mammalian (Chinese hamster lung-derived cells) in vitro assays of mutagenicity, the in vitro CHO/HGPRT assay of mutagenicity, or in vivo clastogenicity assays performed in mice. Tacrolimus did not cause unscheduled DNA synthesis in rodent hepatocytes.

Oral (feed) carcinogenicity studies have been carried out with systemically administered tacrolimus in male and female rats and mice. In the 80-week mouse study and in the 104-week rat study no relationship of tumor incidence to tacrolimus dosage was found at daily doses up to 3 mg/kg [9× the Maximum Recommended Human Dose (MRHD) based on AUC comparisons] and 5 mg/kg (3× the MRHD based on AUC comparisons), respectively.

A 104-week dermal carcinogenicity study was performed in mice with tacrolimus ointment (0.03% - 3%), equivalent to tacrolimus doses of 1.1-118 mg/kg/day or 3.3-354 mg/m^2/day. In the study, the incidence of skin tumors was minimal and the topical application of tacrolimus was not associated with skin tumor formation under ambient room lighting. However, a statistically significant elevation in the incidence of pleomorphic lymphoma in high dose male (25/50) and female animals (27/50) and in the incidence of undifferentiated lymphoma in high dose female animals (13/50) was noted in the mouse dermal carcinogenicity study. Lymphomas were noted in the mouse dermal carcinogenicity study at a daily dose of 3.5 mg/kg (0.1% tacrolimus ointment) (26× MRHD based on AUC comparisons). No drug-related tumors were noted in the mouse dermal carcinogenicity study at a daily dose of 1.1 mg/kg (0.03% tacrolimus ointment) (10× MRHD based on AUC comparisons).

In a 52-week photocarcinogenicity study, the median time to onset of skin tumor formation was decreased in hairless mice following chronic topical dosing with concurrent exposure to UV radiation (40 weeks of treatment followed by 12 weeks of observation) with tacrolimus ointment at ≥0.1% tacrolimus.

Reproductive toxicology studies were not performed with topical tacrolimus. In studies of oral tacrolimus no impairment of fertility was seen in male and female rats. Tacrolimus, given orally at 1.0 mg/kg (0.12× MRHD based on body surface area [BSA]) to male and female rats, prior to and during mating, as well as to dams during gestation and lactation, was associated with embryolethality and with adverse effects on female reproduction. Effects on female reproductive function (parturition) and embryolethal effects were indicated by a higher rate of pre-implantation loss and increased numbers of undelivered and nonviable pups. When given at 3.2 mg/kg (0.43× MRHD based on BSA), tacrolimus was associated with maternal and paternal toxicity as well as reproductive toxicity including marked adverse effects on estrus cycles, parturition, pup viability, and pup malformations.

Pregnancy

Teratogenic Effects:

There are no adequate and well-controlled studies of topically administered tacrolimus in pregnant women. The experience with Tacrolimus Ointment when used by pregnant women is too limited to permit assessment of the safety of its use during pregnancy.

Reproduction studies were carried out with systemically administered tacrolimus in rats and rabbits. Adverse effects on the fetus were observed mainly at oral dose levels that were toxic to dams. Tacrolimus at oral doses of 0.32 and 1.0 mg/kg (0.04×-0.12× MRHD based on BSA) during organogenesis in rabbits was associated with maternal toxicity as well as an increase in incidence of abortions. At the higher dose only, an increased incidence of malformations and developmental variations was also seen. Tacrolimus, at oral doses of 3.2 mg/kg during organogenesis in rats, was associated with maternal toxicity and caused an increase in late resorptions, decreased numbers of live births, and decreased pup weight and viability. Tacrolimus, given orally at 1.0 and 3.2 mg/kg (0.04×-0.12× MRHD based on BSA) to pregnant rats after organogenesis and during lactation, was associated with reduced pup weights.

No reduction in male or female fertility was evident.

There are no adequate and well-controlled studies of systemically administered tacrolimus in pregnant women. Tacrolimus is transferred across the placenta. The use of systemically administered tacrolimus during pregnancy has been associated with neonatal hyperkalemia and renal dysfunction. Tacrolimus Ointment should be used during pregnancy only if the potential benefit to the mother justifies a potential risk to the fetus.

Nursing Mothers

Although systemic absorption of tacrolimus following topical applications of Tacrolimus Ointment is minimal relative to systemic administration, it is known that tacrolimus is excreted in human milk. Because of the potential for serious adverse reactions in nursing infants from tacrolimus, a decision should be made whether to discontinue nursing or to discontinue the drug, taking into account the importance of the drug to the mother.

Pediatric Use

Tacrolimus Ointment is not indicated for children less than 2 years of age.

Only the lower concentration, 0.03%, of Tacrolimus Ointment is recommended for use as a second-line therapy for short-term and non-continuous chronic treatment of moderate to severe atopic dermatitis in non-immunocompromised children 2 to 15 years of age who have failed to respond adequately to other topical prescription treatments for atopic dermatitis, or when those treatments are not advisable.

The long-term safety and effects of Tacrolimus Ointment on the developing immune system are unknown (see boxed WARNING, WARNINGS and INDICATIONS and USAGE).

Four studies were conducted involving a total of about 4,400 patients 2-15 years of age: one 12-week randomized vehicle-controlled study and three open-label safety studies of one to three years duration. About 2,500 of these patients were 2 to 6 years of age.

The most common adverse events from these studies associated with Tacrolimus Ointment application in pediatric patients were skin burning and pruritus (see ADVERSE REACTIONS). In addition to skin burning and pruritus, the less common events (<5%) of varicella zoster (mostly chicken pox), and vesiculobullous rash were more frequent in patients treated with Tacrolimus Ointment 0.03% compared to vehicle. In the open-label safety studies, the incidence of adverse events, including infections, did not increase with increased duration of study drug exposure or amount of ointment used. In about 4,400 pediatric patients treated with Tacrolimus Ointment, 24 (0.5%) were reported with eczema herpeticum. Since the safety and efficacy of Tacrolimus Ointment have not been established in pediatric patients below 2 years of age, its use in this age group is not recommended.

In an open-label study, immune response to a 23-valent pneumococcal polysaccharide vaccine was assessed in 23 children 2 to 12 years old with moderate to severe atopic dermatitis treated with Tacrolimus Ointment 0.03%. Protective antibody titers developed in all patients. Similarly, in a seven-month, double-blind trial, the vaccination response to meningococcal serogroup C was equivalent in children 2 to 11 years old with moderate to severe atopic dermatitis treated with Tacrolimus Ointment 0.03% (n=121), a hydrocortisone ointment regimen (n=111), or normal children (n=44).

Geriatric Use

Four hundred and four (404) patients ≥ 65 years old received Tacrolimus Ointment in phase 3 studies. The adverse event profile for these patients was consistent with that for other adult patients.

ADVERSE REACTIONS

No phototoxicity and no photoallergenicity were detected in clinical studies with 12 and 216 normal volunteers, respectively. One out of 198 normal volunteers showed evidence of sensitization in a contact sensitization study.

In three 12 week randomized vehicle-controlled studies and four safety studies, 655 and 9,163 patients respectively, were treated with Tacrolimus Ointment. The duration of follow-up for adult and pediatric patients in the safety studies is tabulated below.

Duration of Follow-up in Four Open-label Safety Studies
Time on Study | Adult | Pediatrics | Total
< 1 year | 4682 | 4481 | 9163
≥ 1 year | 1185 | 1349 | 2534
≥ 2 years | 200 | 275 | 475
≥ 3 years | 118 | 182 | 300

The following table depicts the adjusted incidence of adverse events pooled across the 3 identically designed 12-week controlled studies for patients in vehicle, Tacrolimus Ointment 0.03%, and Tacrolimus Ointment 0.1% treatment groups. The table also depicts the unadjusted incidence of adverse events in four safety studies, regardless of relationship to study drug.

Incidence of Treatment Emergent Adverse Events
 | 12-Week, Randomized, Double-Blind, Phase 3 Studies 12-Week Adjusted Incidence Rate (%) |  |  |  |  | Open-Label Studies (up to 3 years) 0.1% and 0.03% Tacrolimus Ointment Incidence Rate (%)
 | Adult |  |  | Pediatric |  | Adult | Pediatric | Total
 | Vehicle (n=212) % | 0.03% Tacrolimus Ointment (n=210) % | 0.1% Tacrolimus Ointment (n=209) % | Vehicle (n=116) % | 0.03% Tacrolimus Ointment (n=118) % | (n=4682) % | (n=4481) % | (n=9163) %
Skin Burning [May be reasonably associated with the use of this drug product] | 26 | 46 | 58 | 29 | 43 | 28 | 20 | 24
Pruritus | 37 | 46 | 46 | 27 | 41 | 25 | 19 | 22
Flu-like symptoms | 19 | 23 | 31 | 25 | 28 | 22 | 34 | 28
Allergic Reaction | 8 | 12 | 6 | 8 | 4 | 9 | 13 | 11
Skin Erythema | 20 | 25 | 28 | 13 | 12 | 12 | 7 | 9
Headache | 11 | 20 | 19 | 8 | 5 | 13 | 9 | 11
Skin Infection | 11 | 12 | 5 | 14 | 10 | 9 | 16 | 12
Fever | 4 | 4 | 1 | 13 | 21 | 2 | 14 | 8
Infection | 1 | 1 | 2 | 9 | 7 | 6 | 10 | 8
Cough Increased | 2 | 1 | 1 | 14 | 18 | 3 | 10 | 6
Asthma | 4 | 6 | 4 | 6 | 6 | 4 | 13 | 8
Herpes Simplex | 4 | 4 | 4 | 2 | 0 | 4 | 3 | 3
Eczema Herpeticum | 0 | 1 | 1 | 0 | 2 | 0 | 0 | 0
Pharyngitis | 3 | 3 | 4 | 11 | 6 | 4 | 12 | 8
Accidental Injury | 4 | 3 | 6 | 3 | 6 | 6 | 8 | 7
Pustular Rash | 2 | 3 | 4 | 3 | 2 | 2 | 7 | 5
Folliculitis | 1 | 6 | 4 | 0 | 2 | 4 | 2 | 3
Rhinitis | 4 | 3 | 2 | 2 | 6 | 2 | 4 | 3
Otitis Media | 4 | 0 | 1 | 6 | 12 | 2 | 11 | 6
Sinusitis | 1 | 4 | 2 | 8 | 3 | 6 | 7 | 6
Diarrhea | 3 | 3 | 4 | 2 | 5 | 2 | 4 | 3
Urticaria | 3 | 3 | 6 | 1 | 1 | 3 | 4 | 4
Lack of Drug Effect | 1 | 1 | 0 | 1 | 1 | 6 | 6 | 6
Bronchitis | 0 | 2 | 2 | 3 | 3 | 4 | 4 | 4
Vomiting | 0 | 1 | 1 | 7 | 6 | 1 | 4 | 3
Maculopapular Rash | 2 | 2 | 2 | 3 | 0 | 2 | 1 | 1
Rash | 1 | 5 | 2 | 4 | 2 | 2 | 3 | 3
Abdominal Pain | 3 | 1 | 1 | 2 | 3 | 1 | 3 | 2
Fungal Dermatitis | 0 | 2 | 1 | 3 | 0 | 2 | 4 | 3
Gastroenteritis | 1 | 2 | 2 | 3 | 0 | 2 | 4 | 3
Alcohol Intolerance | 0 | 3 | 7 | 0 | 0 | 4 | 0 | 2
Acne | 2 | 4 | 7 | 1 | 0 | 3 | 2 | 3
Sunburn | 1 | 2 | 1 | 0 | 0 | 2 | 1 | 1
Skin Disorder | 2 | 2 | 1 | 1 | 4 | 2 | 2 | 2
Conjunctivitis | 0 | 2 | 2 | 2 | 1 | 3 | 3 | 3
Pain | 1 | 2 | 1 | 0 | 1 | 2 | 1 | 2
Vesiculobullous Rash | 3 | 3 | 2 | 0 | 4 | 2 | 1 | 1
Lymphadenopathy | 2 | 2 | 1 | 0 | 3 | 1 | 2 | 1
Nausea | 4 | 3 | 2 | 0 | 1 | 2 | 1 | 2
Skin Tingling | 2 | 3 | 8 | 1 | 2 | 2 | 1 | 1
Face Edema | 2 | 2 | 1 | 2 | 1 | 1 | 1 | 1
Dyspepsia | 1 | 1 | 4 | 0 | 0 | 2 | 2 | 2
Dry Skin | 7 | 3 | 3 | 0 | 1 | 1 | 1 | 1
Hyperesthesia | 1 | 3 | 7 | 0 | 0 | 2 | 0 | 1
Skin Neoplasm Benign [Generally "warts".] | 1 | 1 | 1 | 0 | 0 | 1 | 2 | 2
Back Pain | 0 | 2 | 2 | 1 | 1 | 3 | 0 | 2
Peripheral Edema | 2 | 4 | 3 | 0 | 0 | 2 | 0 | 1
Varicella Zoster/Herpes Zoster [All the herpes zoster cases in the pediatric 12-week study and the majority of cases in the open-label pediatric studies were reported as chicken pox.] | 0 | 1 | 0 | 0 | 5 | 1 | 2 | 2
Contact Dermatitis | 1 | 3 | 3 | 3 | 4 | 2 | 2 | 2
Asthenia | 1 | 2 | 3 | 0 | 0 | 1 | 0 | 1
Pneumonia | 0 | 1 | 1 | 2 | 0 | 1 | 3 | 2
Eczema | 2 | 2 | 2 | 0 | 0 | 1 | 0 | 1
Insomnia | 3 | 4 | 3 | 1 | 1 | 2 | 0 | 1
Exfoliative Dermatitis | 3 | 3 | 1 | 0 | 0 | 0 | 1 | 0
Dysmenorrhea | 2 | 4 | 4 | 0 | 0 | 2 | 1 | 1
Periodontal Abscess | 1 | 0 | 1 | 0 | 0 | 1 | 1 | 1
Myalgia | 0 | 3 | 2 | 0 | 0 | 2 | 1 | 1
Cyst | 0 | 1 | 3 | 0 | 0 | 1 | 0 | 1
Cellulitis | 1 | 1 | 1 | 0 | 0 | 1 | 1 | 1
Exacerbation of Untreated Area | 1 | 0 | 1 | 1 | 0 | 1 | 1 | 1
Procedural Complication | 1 | 0 | 0 | 1 | 0 | 1 | 1 | 1
Hypertension | 0 | 0 | 1 | 0 | 0 | 2 | 0 | 1
Tooth Disorder | 0 | 1 | 1 | 1 | 0 | 2 | 1 | 1
Arthralgia | 1 | 1 | 3 | 2 | 0 | 2 | 1 | 2
Depression | 1 | 2 | 1 | 0 | 0 | 1 | 0 | 1
Paresthesia | 1 | 3 | 3 | 0 | 0 | 2 | 1 | 2
Alopecia | 0 | 1 | 1 | 0 | 0 | 1 | 1 | 1
Urinary Tract Infection | 0 | 0 | 1 | 0 | 0 | 2 | 1 | 2
Ear Pain | 1 | 0 | 1 | 0 | 1 | 0 | 1 | 1

Other adverse events which occurred at an incidence between 0.2% and less than 1% in clinical studies in the above table include: abnormal vision, abscess, anaphylactoid reaction, anemia, anorexia, anxiety, arthritis, arthrosis, bilirubinemia, blepharitis, bone disorder, breast neoplasm benign, bursitis, cataract NOS, chest pain, chills, colitis, conjunctival edema, constipation, cramps, cutaneous moniliasis, cystitis, dehydration, dizziness, dry eyes, dry mouth/nose, dyspnea, ear disorder, ecchymosis, edema, epistaxis, eye pain, furunculosis, gastritis, gastrointestinal disorder, hernia, hypercholesterolemia, hypertonia, hypothyroidism, joint disorder, laryngitis, leukoderma, lung disorder, malaise, migraine, moniliasis, mouth ulceration, nail disorder, neck pain, neoplasm benign, oral moniliasis, otitis externa, photosensitivity reaction, rectal disorder, seborrhea, skin carcinoma, skin discoloration, skin hypertrophy, skin ulcer, stomatitis, tendon disorder, thinking abnormal, tooth caries, sweating, syncope, tachycardia, taste perversion, unintended pregnancy, vaginal moniliasis, vaginitis, valvular heart disease, vasodilatation, and vertigo.

Post-Marketing Events

The following adverse reactions have been identified during postapproval use of Tacrolimus Ointment. Because these reactions are reported voluntarily from a population of uncertain size, it is not always possible to reliably estimate their frequency or establish a causal relationship to drug exposure.

CNS

Seizures

Neoplasms

Lymphomas, basal cell carcinoma, squamous cell carcinoma, malignant melanoma

Infections

Bullous impetigo, osteomyelitis, septicemia

Renal

Acute renal failure in patients with or without Netherton's syndrome, renal impairment

Skin

Rosacea, application site edema

OVERDOSAGE

Tacrolimus Ointment is not for oral use. Oral ingestion of Tacrolimus Ointment may lead to adverse effects associated with systemic administration of tacrolimus. If oral ingestion occurs, medical advice should be sought.

DOSAGE AND ADMINISTRATION

Adult

Tacrolimus Ointment 0.03% and 0.1%

- Apply a thin layer of Tacrolimus Ointment to the affected skin twice daily. The minimum amount should be rubbed in gently and completely to control signs and symptoms of atopic dermatitis. Stop using when signs and symptoms of atopic dermatitis resolve.
- If signs and symptoms (e.g. itch, rash, and redness) do not improve within 6 weeks, patients should be re-examined by their healthcare provider to confirm the diagnosis of atopic dermatitis.
- Continuous long-term use of topical calcineurin inhibitors, including Tacrolimus Ointment should be avoided, and application should be limited to areas of involvement with atopic dermatitis.

The safety of Tacrolimus Ointment under occlusion, which may promote systemic exposure, has not been evaluated. Tacrolimus Ointment should not be used with occlusive dressings.

Pediatric – For Children 2-15 Years

Tacrolimus Ointment 0.03%

- Apply a thin layer of Tacrolimus Ointment, 0.03% to the affected skin twice daily. The minimum amount should be rubbed in gently and completely to control signs and symptoms of atopic dermatitis. Stop using when signs and symptoms of atopic dermatitis resolve.
- If signs and symptoms (e.g. itch, rash, and redness) do not improve within 6 weeks, patients should be re-examined by their healthcare provider to confirm the diagnosis of atopic dermatitis.
- Continuous long-term use of topical calcineurin inhibitors, including Tacrolimus Ointment should be avoided, and application should be limited to areas of involvement with atopic dermatitis.

The safety of Tacrolimus Ointment under occlusion, which may promote systemic exposure, has not been evaluated. Tacrolimus Ointment should not be used with occlusive dressings.

HOW SUPPLIED

Tacrolimus Ointment 0.03%

NDC 45802-390-00
30 gram laminate tube

NDC 45802-390-01
60 gram laminate tube

NDC 45802-390-02
100 gram laminate tube

Tacrolimus Ointment 0.1%

NDC 45802-700-00
30 gram laminate tube

NDC 45802-700-01
60 gram laminate tube

NDC 45802-700-02
100 gram laminate tube

STORAGE AND HANDLING

Store at room temperature 25°C (77°F); excursions permitted to 15°-30°C (59°-86°F).

Manufactured by:
LEO Laboratories Ltd.
285 Cashel Road
Dublin 12, Ireland

Distributed by:
Padagis
Allegan, MI 49010
www.padagis.com

Revised: 12/2022

MEDICATION GUIDE Tacrolimus Ointment 0.03% Ointment 0.1%

Read the Medication Guide every time you or a family member gets Tacrolimus Ointment. There may be new information. This Medication Guide does not take the place of talking to your doctor about your medical condition or treatment. If you have questions about Tacrolimus Ointment, ask your doctor or pharmacist.

What is the most important information I should know about Tacrolimus Ointment?

The safety of using Tacrolimus Ointment for a long period of time is not known. A very small number of people who have used Tacrolimus Ointment have had cancer (for example, skin or lymphoma). However, a link with Tacrolimus Ointment has not been shown. Because of this concern:

- Do not use Tacrolimus Ointment continuously for a long time.
- Use Tacrolimus Ointment only on areas of your skin that have eczema.
- Do not use Tacrolimus Ointment on a child under 2 years old.

Tacrolimus Ointment comes in two strengths:

- Only Tacrolimus Ointment 0.03% is for use on children aged 2 to 15 years.
- Either Tacrolimus Ointment 0.03% or 0.1% can be used by adults and children 16 years and older.

Talk to your doctor for more information.

What is Tacrolimus Ointment?

Tacrolimus Ointment is a prescription medicine used on the skin (topical) to treat eczema (atopic dermatitis). Tacrolimus Ointment is in a class of medicines called topical calcineurin inhibitors. It is for adults and children 2 years of age and older who do not have a weakened immune system. Tacrolimus Ointment is used on the skin for short periods, and if needed, treatment may be repeated with breaks in between.

Tacrolimus Ointment is for use after other prescription medicines have not worked for you, or if your doctor recommends that other prescription medicines should not be used.

Who should not use Tacrolimus Ointment?

Tacrolimus Ointment should not be used:

- on children younger than 2 years of age.
- if you are allergic to Tacrolimus Ointment or anything in it. See the end of this Medication Guide for a complete list of ingredients.

What should I tell my doctor before starting Tacrolimus Ointment?

Before you start using Tacrolimus Ointment, you and your doctor should talk about all of your medical conditions, including if you:

- have a skin disease called Netherton's syndrome (a rare inherited condition).
- have any infection on your skin including chicken pox or herpes.
- have been told you have a weakened immune system.
- are pregnant, breastfeeding, or planning to become pregnant.

Tell your doctor about all the medicines you take and skin products you use including prescription and nonprescription medicines, vitamins, and herbal supplements.

Know the medicines you take. Keep a list of them with you to show your doctor and pharmacist each time you get a new medicine.

How should I use Tacrolimus Ointment?

- Use Tacrolimus Ointment exactly as prescribed.
- Use Tacrolimus Ointment only on areas of your skin that have eczema.
- Use Tacrolimus Ointment for short periods, and if needed, treatment may be repeated with breaks in between.
- Stop Tacrolimus Ointment when the signs and symptoms of eczema, such as itching, rash, and redness go away, or as directed by your doctor.
- Follow your doctor's advice if symptoms of eczema return after treatment with Tacrolimus Ointment.
- Call your doctor if :
  - your symptoms get worse with Tacrolimus Ointment.
  - you get an infection on your skin.
  - your symptoms do not improve after 6 weeks of treatment. Sometimes other skin diseases can look like eczema.

To apply Tacrolimus Ointment:

- Wash your hands before applying Tacrolimus Ointment.
- Apply a thin layer of Tacrolimus Ointment twice daily to the areas of skin affected by eczema.
- Use the smallest amount of Tacrolimus Ointment needed to control the signs and symptoms of eczema.
- If you are a caregiver applying Tacrolimus Ointment to a patient, or if you are a patient who is not treating your hands, wash your hands with soap and water after applying Tacrolimus Ointment. This should remove any ointment left on the hands.
- Do not bathe, shower, or swim right after applying Tacrolimus Ointment. This could wash off the ointment.
- You can use moisturizers with Tacrolimus Ointment. Make sure you check with your doctor first about the products that are right for you. Because the skin of patients with eczema can be very dry, it is important to keep up good skin care practices. If you use moisturizers, apply them after Tacrolimus Ointment.

What should I avoid while using Tacrolimus Ointment?

- Do not use ultraviolet light therapy, sun lamps, or tanning beds during treatment with Tacrolimus Ointment.
- Limit sun exposure during treatment with Tacrolimus Ointment even when the medicine is not on your skin. If you need to be outdoors after applying Tacrolimus Ointment, wear loose fitting clothing that protects the treated area from the sun. Ask your doctor what other types of protection from the sun you should use.
- Do not cover the skin being treated with bandages, dressings or wraps. You can wear normal clothing.
- Avoid getting Tacrolimus Ointment in the eyes or mouth. Do not swallow Tacrolimus Ointment. If you do, call your doctor.

What are the possible side effects of Tacrolimus Ointment?

Please read the first section of this Medication Guide.

The most common side effects of Tacrolimus Ointment at the skin application site are stinging, burning, or itching of the skin treated with Tacrolimus. These side effects are usually mild to moderate, are most common during the first few days of treatment, and usually go away as your skin heals.

Other side effects include acne, swollen or infected hair follicles, headache, increased sensitivity of the skin to hot or cold temperatures, or flu-like symptoms such as the common cold and stuffy nose, skin tingling, upset stomach, muscle pain, swollen glands (enlarged lymph nodes), or skin infections including cold sores, chicken pox or shingles.

Talk to your doctor if you have a skin infection or if side effects (for example, swollen glands) continue or bother you.

While you are using Tacrolimus, drinking alcohol may cause the skin or face to become flushed or red and feel hot.

These are not all the side effects with Tacrolimus Ointment. Ask your doctor or pharmacist for more information.

Call your doctor for medical advice about side effects. You may report side effects to FDA at 1-800-FDA-1088

How should I store Tacrolimus Ointment?

- Store Tacrolimus Ointment at room temperature (59° to 86°F). Do not leave Tacrolimus Ointment in your car in cold or hot weather. Make sure the cap on the tube is tightly closed.
- Keep Tacrolimus Ointment and all medicines out of the reach of children.

General advice about Tacrolimus Ointment

Medicines are sometimes prescribed for purposes other than those listed in a Medication Guide. Do not use Tacrolimus Ointment for a condition for which it was not prescribed. Do not give Tacrolimus Ointment to other people, even if they have the same symptoms you have. It may not be right for them.

This Medication Guide summarizes the most important information about Tacrolimus Ointment. If you would like more information, talk with your doctor.

Your doctor or pharmacist can give you information about Tacrolimus Ointment that is written for health care professionals. For more information, you can call Perrigo at 1-866-634-9120.

What are the ingredients in Tacrolimus Ointment?

Active Ingredient: tacrolimus, either 0.03% or 0.1%
Inactive Ingredients: mineral oil, paraffin, propylene carbonate, white petrolatum, white wax, all-rac-α-tocopherol and butylhydroxytoluene.

Manufactured by:
LEO Laboratories Ltd.
285 Cashel Road
Dublin 12, Ireland

Distributed by:
Padagis
Allegan, MI 49010
www.padagis.com

This Medication Guide has been approved by the U.S. Food and Drug Administration.

Revised: 12/2022

PRINCIPLE DISPLAY PANEL - 30 g Tube Carton - NDC 45802-390-00

NDC 45802-390-00

Rx Only

Tacrolimus Ointment 0.03%
Attention: Dispense with enclosed Medication Guide

30 g

Padagis™

PRINCIPLE DISPLAY PANEL - 30 g Tube Carton - NDC 45802-700-00

NDC 45802-700-00

Rx Only

Tacrolimus Ointment 0.1%
Attention: Dispense with enclosed Medication Guide

30 g

Padagis™